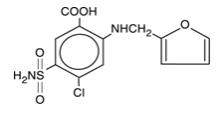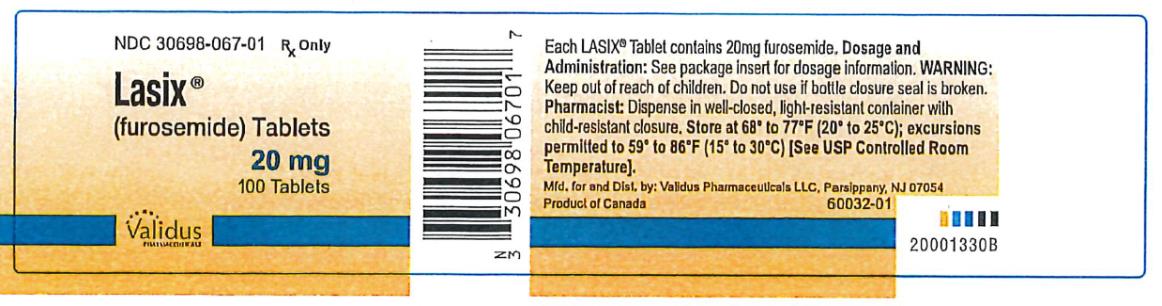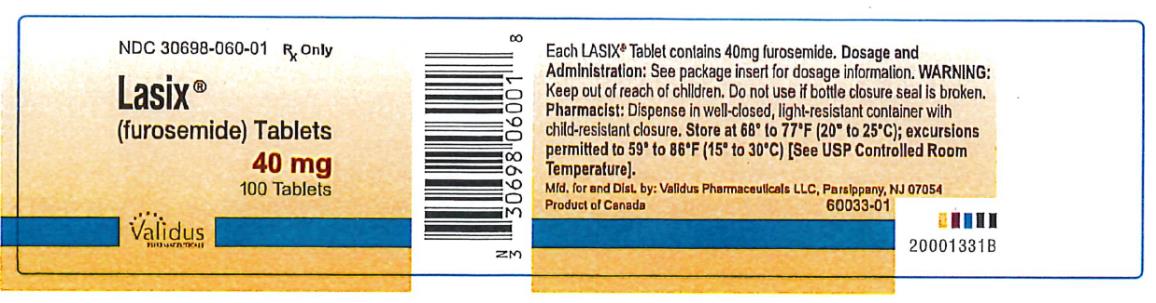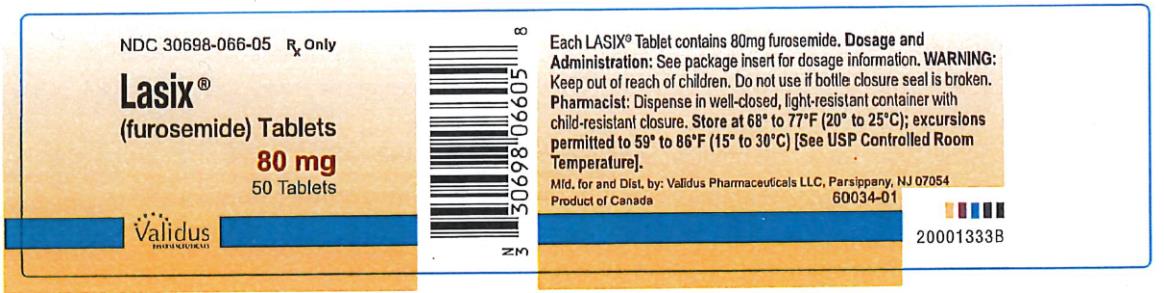 DRUG LABEL: Lasix
NDC: 30698-067 | Form: TABLET
Manufacturer: Validus Pharmaceuticals LLC
Category: prescription | Type: HUMAN PRESCRIPTION DRUG LABEL
Date: 20250930

ACTIVE INGREDIENTS: FUROSEMIDE 20 mg/1 1
INACTIVE INGREDIENTS: LACTOSE MONOHYDRATE; MAGNESIUM STEARATE; STARCH, CORN; TALC; SILICON DIOXIDE

Lasix

LASIX® (furosemide) Tablets 20, 40, and 80mg

Rx Only

WARNING

LASIX® (furosemide) is a potent diuretic which, if given in excessive amounts, can lead to a profound diuresis with water and electrolyte depletion. Therefore, careful medical supervision is required and dose and dose schedule must be adjusted to the individual patient’s needs (see DOSAGE AND ADMINISTRATION).

DESCRIPTION

LASIX®is a diuretic which is an anthranilic acid derivative. LASIX tablets for oral administration contain furosemide as the active ingredient and the following inactive ingredients: lactose monohydrate NF, magnesium stearate NF, starch NF, talc USP, and colloidal silicon dioxide NF. Chemically, it is 4-chloro-N-furfuryl-5-sulfamoylanthranilic acid. LASIX is available as white tablets for oral administration in dosage strengths of 20, 40 and 80mg. Furosemide is a white to off-white odorless crystalline powder. It is practically insoluble in water, sparingly soluble in alcohol, freely soluble in dilute alkali solutions and insoluble in dilute acids.

The CAS Registry Number is 54-31-9.

The structural formula is as follows:

CLINICAL PHARMACOLOGY

Investigations into the mode of action of LASIX have utilized micropuncture studies in rats, stop flow experiments in dogs and various clearance studies in both humans and experimental animals. It has been demonstrated that LASIX inhibits primarily the absorption of sodium and chloride not only in the proximal and distal tubu but also in the loop of Henle. The high degree of efficacy is largely due to the unique site of action. The action on the distal tubule is independent of any inhibitory effect on carbonic anhydrase and aldosterone.

Recent evidence suggests that furosemide glucuronide is the only or at least the major biotransformation product of furosemide in man. Furosemide is extensively bound to plasma proteins, mainly to albumin. Plasma concentrations ranging from 1 μg/mL to 400 μg/mL are 91% to 99% bound in healthy individuals. The unbound fraction averages 2.3% to 4.1% at therapeutic concentrations.

The onset of diuresis following oral administration is within 1 hour. The peak effect occurs within the first or second hour. The duration of diuretic effect is 6 to 8 hours.

In fasted normal men, the mean bioavailability of furosemide from LASIX Tablets and LASIX Oral Solution is 64% and 60%, respectively, of that from an intravenous injection of the drug. Although furosemide is more rapidly absorbed from the oral solution (50 minutes) than from the tablet (87 minutes), peak plasma levels and area under the plasma concentration-time curves do not differ significantly. Peak plasma concentrations increase with increasing dose but times-to-peak do not differ among doses. The terminal half-life of furosemide is approximately 2 hours.

Significantly more furosemide is excreted in urine following the IV injection than after the tablet or oral solution. There are no significant differences between the two oral formulations in the amount of unchanged drug excreted in urine.

Geriatric Population

Furosemide binding to albumin may be reduced in elderly patients. Furosemide is predominantly excreted unchanged in the urine. The renal clearance of furosemide after intravenous administration in older healthy male subjects (60 to 70 years of age) is statistically significantly smaller than in younger healthy male subjects (20 to 35 years of age). The initial diuretic effect of furosemide in older subjects is decreased relative to younger subjects (see PRECAUTIONS: Geriatric Use).

INDICATIONS AND USAGE

Edema

LASIX is indicated in adults and pediatric patients for the treatment of edema associated with congestive heart failure, cirrhosis of the liver, and renal disease, including the nephrotic syndrome. LASIX is particularly useful when an agent with greater diuretic potential is desired.

Hypertension

Oral LASIX may be used in adults for the treatment of hypertension alone or in combination with other antihypertensive agents. Hypertensive patients who cannot be adequately controlled with thiazides will probably also not be adequately controlled with LASIX alone.

CONTRAINDICATIONS

LASIX is contraindicated in patients with anuria and in patients with a history of hypersensitivity to furosemide.

WARNINGS

In patients with hepatic cirrhosis and ascites, LASIX therapy is best initiated in the hospital. In hepatic coma and in states of electrolyte depletion, therapy should not be instituted until the basic condition is improved. Sudden alterations of fluid and electrolyte balance in patients with cirrhosis may precipitate hepatic coma; therefore, strict observation is necessary during the period of diuresis. Supplemental potassium chloride and, if required, an aldosterone antagonist are helpful in preventing hypokalemia and metabolic alkalosis.

If increasing azotemia and oliguria occur during treatment of severe progressive renal disease, LASIX should be discontinued.

Cases of tinnitus and reversible or irreversible hearing impairment and deafness have been reported. Reports usually indicate that LASIX ototoxicity is associated with rapid injection, severe renal impairment, the use of higher than recommended doses, hypoproteinemia or concomitant therapy with aminoglycoside antibiotics, ethacrynic acid, or other ototoxic drugs. If the physician elects to use high dose parenteral therapy, controlled intravenous infusion is advisable (for adults, an infusion rate not exceeding 4mg LASIX per minute has been used) (see PRECAUTIONS: Drug Interactions).

PRECAUTIONS

General

Excessive diuresis may cause dehydration and blood volume reduction with circulatory collapse and possibly vascular thrombosis and embolism, particularly in elderly patients. As with any effective diuretic, electrolyte depletion may occur during LASIX therapy, especially in patients receiving higher doses and a restricted salt intake. Hypokalemia may develop with LASIX, especially with brisk diuresis, inadequate oral electrolyte intake, when cirrhosis is present, or during concomitant use of corticosteroids, ACTH, licorice in large amounts, or prolonged use of laxatives. Digitalis therapy may exaggerate metabolic effects of hypokalemia, especially myocardial effects.

All patients receiving LASIX therapy should be observed for these signs or symptoms of fluid or electrolyte imbalance (hyponatremia, hypochloremic alkalosis, hypokalemia, hypomagnesemia or hypocalcemia): dryness of mouth, thirst, weakness, lethargy, drowsiness, restlessness, muscle pains or cramps, muscular fatigue, hypotension, oliguria, tachycardia, arrhythmia, or gastrointestinal disturbances such as nausea and vomiting. Increases in blood glucose and alterations in glucose tolerance tests (with abnormalities of the fasting and 2-hour postprandial sugar) have been observed, and rarely, precipitation of diabetes mellitus has been reported.

In patients with severe symptoms of urinary retention (because of bladder emptying disorders, prostatic hyperplasia, urethral narrowing), the administration of furosemide can cause acute urinary retention related to increased production and retention of urine. Thus, these patients require careful monitoring, especially during the initial stages of treatment.

In patients at high risk for radiocontrast nephropathy, LASIX can lead to a higher incidence of deterioration in renal function after receiving radiocontrast compared to high-risk patients who received only intravenous hydration prior to receiving radiocontrast.

In patients with hypoproteinemia (e.g., associated with nephrotic syndrome), the effect of LASIX may be weakened and its ototoxicity potentiated.

Asymptomatic hyperuricemia can occur and gout may rarely be precipitated.

Patients allergic to sulfonamides may also be allergic to LASIX. The possibility exists of exacerbation or activation of systemic lupus erythematosus.

As with many other drugs, patients should be observed regularly for the possible occurrence of blood dyscrasias, liver or kidney damage, or other idiosyncratic reactions.

Information for Patients

Patients receiving LASIX should be advised that they may experience symptoms from excessive fluid and/or electrolyte losses. The postural hypotension that sometimes occurs can usually be managed by getting up slowly. Potassium supplements and/or dietary measures may be needed to control or avoid hypokalemia.

Patients with diabetes mellitus should be told that furosemide may increase blood glucose levels and thereby affect urine glucose tests. The skin of some patients may be more sensitive to the effects of sunlight while taking furosemide.

Hypertensive patients should avoid medications that may increase blood pressure, including over-the-counter products for appetite suppression and cold symptoms.

Laboratory Tests

Serum electrolytes (particularly potassium), CO2, creatinine and BUN should be determined frequently during the first few months of LASIX therapy and periodically thereafter. Serum and urine electrolyte determinations are particularly important when the patient is vomiting profusely or receiving parenteral fluids. Abnormalities should be corrected or the drug temporarily withdrawn. Other medications may also influence serum electrolytes.

Reversible elevations of BUN may occur and are associated with dehydration, which should be avoided, particularly in patients with renal insufficiency.

Urine and blood glucose should be checked periodically in diabetics receiving LASIX, even in those suspected of latent diabetes.

LASIX may lower serum levels of calcium (rarely cases of tetany have been reported) and magnesium. Accordingly, serum levels of these electrolytes should be determined periodically.

In premature infants LASIX may precipitate nephrocalcinosis/nephrolithiasis, therefore renal function must be monitored and renal ultrasonography performed (see PRECAUTIONS: Pediatric Use).

Drug Interactions

LASIX may increase the ototoxic potential of aminoglycoside antibiotics, especially in the presence of impaired renal function. Except in life-threatening situations, avoid this combination.

LASIX should not be used concomitantly with ethacrynic acid because of the possibility of ototoxicity. Patients receiving high doses of salicylates concomitantly with LASIX, as in rheumatic disease, may experience salicylate toxicity at lower doses because of competitive renal excretory sites.

There is a risk of ototoxic effects if cisplatin and LASIX are given concomitantly. In addition, nephrotoxicity of nephrotoxic drugs such as cisplatin may be enhanced if LASIX is not given in lower doses and with positive fluid balance when used to achieve forced diuresis during cisplatin treatment.

LASIX has a tendency to antagonize the skeletal muscle-relaxing effect of tubocurarine and may potentiate the action of succinylcholine.

Lithium generally should not be given with diuretics because they reduce lithium’s renal clearance and add a high risk of lithium toxicity.

LASIX combined with angiotensin-converting enzyme inhibitors or angiotensin II receptor blockers may lead to severe hypotension and deterioration in renal function, including renal failure. An interruption or reduction in the dosage of LASIX, angiotensin-converting enzyme inhibitors, or angiotensin receptor blockers may be necessary.

Potentiation occurs with ganglionic or peripheral adrenergic blocking drugs.

LASIX may decrease arterial responsiveness to norepinephrine. However, norepinephrine may still be used effectively.

Simultaneous administration of sucralfate and LASIX tablets may reduce the natriuretic and antihypertensive effects of LASIX. Patients receiving both drugs should be observed closely to determine if the desired diuretic and/or antihypertensive effect of LASIX is achieved. The intake of LASIX and sucralfate should be separated by at least two hours.

In isolated cases, intravenous administration of LASIX within 24 hours of taking chloral hydrate may lead to flushing, sweating attacks, restlessness, nausea, increase in blood pressure, and tachycardia. Use of LASIX concomitantly with chloral hydrate is therefore not recommended.

Phenytoin interferes directly with renal action of LASIX. There is evidence that treatment with phenytoin leads to decreased intestinal absorption of LASIX, and consequently to lower peak serum furosemide concentrations.

Methotrexate and other drugs that, like LASIX, undergo significant renal tubular secretion may reduce the effect of LASIX. Conversely, LASIX may decrease renal elimination of other drugs that undergo tubular secretion. High-dose treatment of both LASIX and these other drugs may result in elevated serum levels of these drugs and may potentiate their toxicity as well as the toxicity of LASIX.

LASIX can increase the risk of cephalosporin-induced nephrotoxicity even in the setting of minor or transient renal impairment.

Concomitant use of cyclosporine and LASIX is associated with increased risk of gouty arthritis secondary to LASIX-induced hyperurecemia and cyclosporine impairment of renal urate excretion.

High doses (>80mg) of furosemide may inhibit the binding of thyroid hormones to carrier proteins and result in transient increase in free thyroid hormones, followed by an overall decrease in total thyroid hormone levels.

One study in six subjects demonstrated that the combination of furosemide and acetylsalicylic acid temporarily reduced creatinine clearance in patients with chronic renal insufficiency. There are case reports of patients who developed increased BUN, serum creatinine and serum potassium levels, and weight gain when furosemide was used in conjunction with NSAIDs.

Literature reports indicate that coadministration of indomethacin may reduce the natriuretic and antihypertensive effects of LASIX (furosemide) in some patients by inhibiting prostaglandin synthesis. Indomethacin may also affect plasma renin levels, aldosterone excretion, and renin profile evaluation. Patients receiving both indomethacin and LASIX should be observed closely to determine if the desired diuretic and/or antihypertensive effect of LASIX is achieved.

Carcinogenesis, Mutagenesis, Impairment of Fertility

Furosemide was tested for carcinogenicity by oral administration in one strain of mice and one strain of rats. A small but significantly increased incidence of mammary gland carcinomas occurred in female mice at a dose 17.5 times the maximum human dose of 600mg. There were marginal increases in uncommon tumors in male rats at a dose of 15 mg/kg (slightly greater than the maximum human dose) but not at 30 mg/kg.

Furosemide was devoid of mutagenic activity in various strains of Salmonella typhimuriumwhen tested in the presence or absence of an in vitrometabolic activation system, and questionably positive for gene mutation in mouse lymphoma cells in the presence of rat liver S9 at the highest dose tested. Furosemide did not induce sister chromatid exchange in human cells in vitro, but other studies on chromosomal aberrations in human cells in vitrogave conflicting results. In Chinese hamster cells it induced chromosomal damage but was questionably positive for sister chromatid exchange. Studies on the induction by furosemide of chromosomal aberrations in mice were inconclusive. The urine of rats treated with this drug did not induce gene conversion in Saccharomyces cerevisiae.

LASIX (furosemide) produced no impairment of fertility in male or female rats, at 100 mg/kg/day (the maximum effective diuretic dose in the rat and 8 times the maximal human dose of 600 mg/day).

Pregnancy

Furosemide has been shown to cause unexplained maternal deaths and abortions in rabbits at 2, 4 and 8 times the maximal recommended human dose. There are no adequate and well-controlled studies in pregnant women. LASIX should be used during pregnancy only if the potential benefit justifies the potential risk to the fetus.

Treatment during pregnancy requires monitoring of fetal growth because of the potential for higher birth weights.

The effects of furosemide on embryonic and fetal development and on pregnant dams were studied in mice, rats and rabbits.

Furosemide caused unexplained maternal deaths and abortions in the rabbit at the lowest dose of 25 mg/kg (2 times the maximal recommended human dose of 600 mg/day). In another study, a dose of 50 mg/kg (4 times the maximal recommended human dose of 600 mg/day) also caused maternal deaths and abortions when administered to rabbits between Days 12 and 17 of gestation. In a third study, none of the pregnant rabbits survived a dose of 100 mg/kg. Data from the above studies indicate fetal lethality that can precede maternal deaths.

The results of the mouse study and one of the three rabbit studies also showed an increased incidence and severity of hydronephrosis (distention of the renal pelvis and, in some cases, of the ureters) in fetuses derived from the treated dams as compared with the incidence in fetuses from the control group.

Nursing Mothers

Because it appears in breast milk, caution should be exercised when LASIX is administered to a nursing mother.

LASIX may inhibit lactation.

Pediatric Use

In premature infants LASIX may precipitate nephrocalcinosis/nephrolithiasis. Nephrocalcinosis/nephrolithiasis has also been observed in children under 4 years of age with no history of prematurity who have been treated chronically with LASIX. Monitor renal function, and renal ultrasonography should be considered, in pediatric patients receiving LASIX.

If LASIX is administered to premature infants during the first weeks of life, it may increase the risk of persistence of patent ductus arteriosus.

Geriatric Use

Controlled clinical studies of LASIX did not include sufficient numbers of subjects aged 65 and over to determine whether they respond differently from younger subjects. Other reported clinical experience has not identified differences in responses between the elderly and younger patients. In general, dose selection for the elderly patient should be cautious, usually starting at the low end of the dosing range, reflecting the greater frequency of decreased hepatic, renal, or cardiac function, and of concomitant disease or other drug therapy.

This drug is known to be substantially excreted by the kidney, and the risk of toxic reactions to this drug may be greater in patients with impaired renal function. Because elderly patients are more likely to have decreased renal function, care should be taken in dose selection and it may be useful to monitor renal function (see PRECAUTIONS: Generaland DOSAGE AND ADMINISTRATION).

ADVERSE REACTIONS

Adverse reactions are categorized below by organ system and listed by decreasing severity.

Gastrointestinal System Reactions
1. hepatic encephalopathy in patients with hepatocellular insufficiency | 6. oral and gastric irritation 7. cramping
2. pancreatitis | 8. diarrhea
3. jaundice (intrahepatic cholestatic jaundice) | 9. constipation
4. increased liver enzymes | 10. nausea
5. anorexia | 11. vomiting
Systemic Hypersensitivity Reactions
1. Severe anaphylactic or anaphylactoid reactions (e.g., with shock) | 3. interstitial nephritis 4. necrotizing angiitis
2. systemic vasculitis
Central Nervous System Reactions
1. tinnitus and hearing loss | 5. headache
2. paresthesias | 6. blurred vision
3. vertigo | 7. xanthopsia
4. dizziness
Hematologic Reactions
1. aplastic anemia | 5. leukopenia
2. thrombocytopenia | 6. anemia
3. agranulocytosis | 7. eosinophilia
4. hemolytic anemia
Dermatologic-Hypersensitivity Reactions
1. toxic epidermal necrolysis | 7. bullous pemphigoid
2. Stevens-Johnson Syndrome 3. erythema multiforme | 8. purpura 9. photosensitivity
4. drug rash with eosinophilia and systemic symptoms | 10. rash 11. pruritis
5. acute generalized exanthematous pustulosis 6. exfoliative dermatitis | 12. urticaria
Cardiovascular Reaction
1. Orthostatic hypotension may occur and be aggravated by alcohol, barbiturates, or narcotics.
2. Increase in cholesterol and triglyceride serum levels
Other Reactions
1. hyperglycemia | 6. restlessness
2. glycosuria | 7. urinary bladder spasm
3. hyperuricemia | 8. thrombophlebitis
4. muscle spasm | 9. fever
5. weakness

Whenever adverse reactions are moderate or severe, LASIX dosage should be reduced or therapy withdrawn.

To report SUSPECTED ADVERSE REACTIONS, contact Validus Pharmaceuticals LLC at

1-866-982-5438 (1-866-9VALIDUS) or FDA at 1-800-FDA-1088 or www.fda.gov/medwatch.

OVERDOSAGE

The principal signs and symptoms of overdose with LASIX are dehydration, blood volume reduction, hypotension, electrolyte imbalance, hypokalemia and hypochloremic alkalosis, and are extensions of its diuretic action.

The acute toxicity of LASIX has been determined in mice, rats and dogs. In all three, the oral LD50exceeded 1000 mg/kg body weight, while the intravenous LD50ranged from 300 to 680 mg/kg.

The acute intragastric toxicity in neonatal rats is 7 to 10 times that of adult rats.

The concentration of LASIX in biological fluids associated with toxicity or death is not known.

Treatment of overdosage is supportive and consists of replacement of excessive fluid and electrolyte losses. Serum electrolytes, carbon dioxide level and blood pressure should be determined frequently. Adequate drainage must be assured in patients with urinary bladder outlet obstruction (such as prostatic hypertrophy).

Hemodialysis does not accelerate furosemide elimination.

DOSAGE AND ADMINISTRATION

Edema

Therapy should be individualized according to patient response to gain maximal therapeutic response and to determine the minimal dose needed to maintain that response.

Adults-- The usual initial dose of LASIX is 20 mg to 80mg given as a single dose. Ordinarily a prompt diuresis ensues. If needed, the same dose can be administered 6 to 8 hours later or the dose may be increased. The dose may be raised by 20 mg or 40mg and given not sooner than 6 to 8 hours after the previous dose until the desired diuretic effect has been obtained. The individually determined single dose should then be given once or twice daily (e.g., at 8 am and 2 pm). The dose of LASIX may be carefully titrated up to 600 mg/day in patients with clinically severe edematous states.

Edema may be most efficiently and safely mobilized by giving LASIX on 2 to 4 consecutive days each week.

When doses exceeding 80 mg/day are given for prolonged periods, careful clinical observation and laboratory monitoring are particularly advisable (see PRECAUTIONS: Laboratory Test).

Geriatric patients-- In general, dose selection for the elderly patient should be cautious, usually starting at the low end of the dosing range (see PRECAUTIONS: Geriatric Use).

Pediatric patients-- The usual initial dose of oral LASIX in pediatric patients is 2 mg/kg body weight, given as a single dose. If the diuretic response is not satisfactory after the initial dose, dosage may be increased by 1 or 2 mg/kg no sooner than 6 to 8 hours after the previous dose. Doses greater than 6 mg/kg body weight are not recommended. For maintenance therapy in pediatric patients, the dose should be adjusted to the minimum effective level.

Hypertension

Therapy should be individualized according to the patient’s response to gain maximal therapeutic response and to determine the minimal dose needed to maintain the therapeutic response.

Adults-- The usual initial dose of LASIX for hypertension is 80mg, usually divided into 40mg twice a day. Dosage should then be adjusted according to response. If response is not satisfactory, add other antihypertensive agents.

Changes in blood pressure must be carefully monitored when LASIX is used with other antihypertensive drugs, especially during initial therapy. To prevent excessive drop in blood pressure, the dosage of other agents should be reduced by at least 50% when LASIX is added to the regimen. As the blood pressure falls under the potentiating effect of LASIX, a further reduction in dosage or even discontinuation of other antihypertensive drugs may be necessary.

Geriatric patients-- In general, dose selection and dose adjustment for the elderly patient should be cautious, usually starting at the low end of the dosing range (see PRECAUTIONS: Geriatric Use).

HOW SUPPLIED

LASIX (furosemide) Tablets 20mg are supplied as white, oval, monogrammed tablets in Bottles of 100 (NDC 30698-067-01) and 1000 (NDC 30698-067-10). The 20mg tablets are imprinted with “Lasix®” on one side.

LASIX Tablets 40mg are supplied as white, round, monogrammed, scored tablets in Bottles of 100 (NDC 30698-060-01), 500 (NDC 30698-060-50), and 1000 (NDC 30698-060-10). The 40mg tablets are imprinted with “Lasix®40” on one side.

LASIX Tablets 80mg are supplied as white, round, scored, monogrammed, facetted-edge tablets in Bottles of 50 (NDC 30698-066-05) and 500 (NDC 30698-066-50). The 80mg tablets are imprinted with “Lasix®80” on one side.

Note: Dispense in well-closed, light-resistant containers. Exposure to light might cause a slight discoloration. Discolored tablets should not be dispensed.

Tested by USP Dissolution Test 2

Store at 68º to 77ºF (20º to 25ºC); excursions permitted to 59º to 86ºF (15º to 30ºC) [See USP Controlled Room Temperature].

Manufactured for and Distributed by:
Validus Pharmaceuticals LLC
Parsippany, NJ 07054
info@validuspharma.com
www.validuspharma.com
1-866-982-5438

Product of Canada

© 2018 Validus Pharmaceuticals LLC

60031-05 August 2018

PRINCIPAL DISPLAY PANEL

NDC 30698-067-01
Lasix®
(furosemide)Tablets
20 mg
100 Tablets
Rx Only

PRINCIPAL DISPLAY PANEL

NDC 30698-060-01
Lasix®
(furosemide)Tablets
40 mg
100 Tablets
Rx Only

PRINCIPAL DISPLAY PANEL

NDC 30698-066-05
Lasix®
(furosemide)Tablets
80 mg
50 Tablets
Rx Only